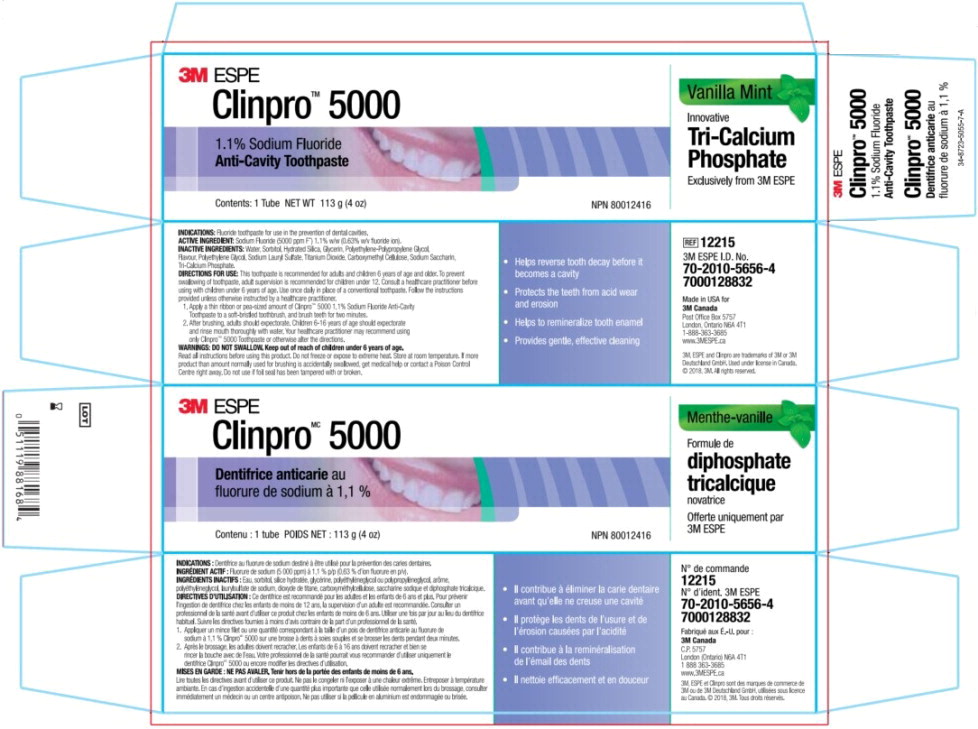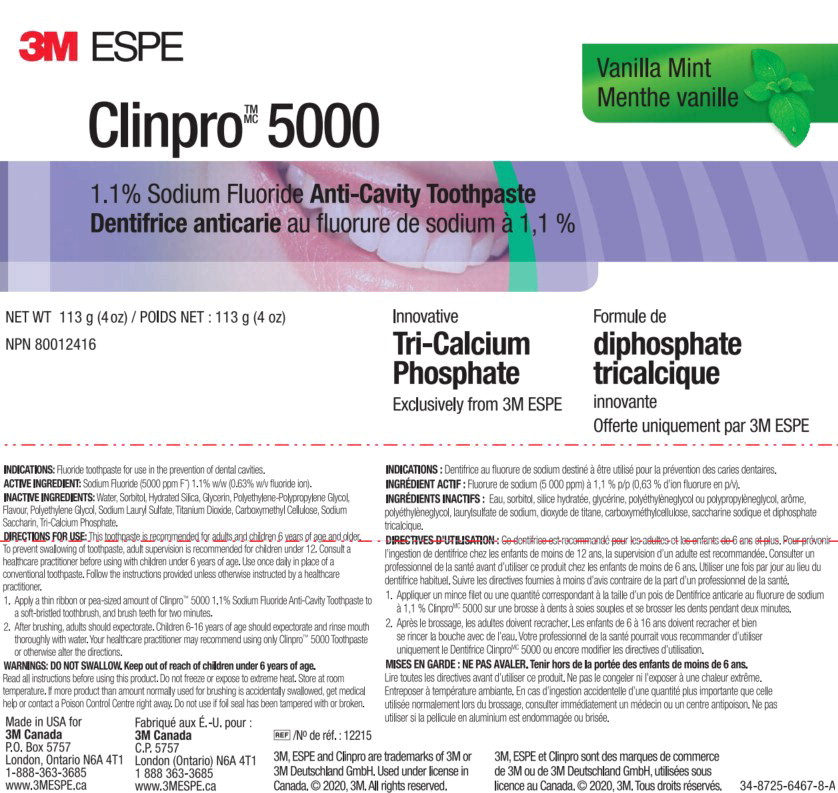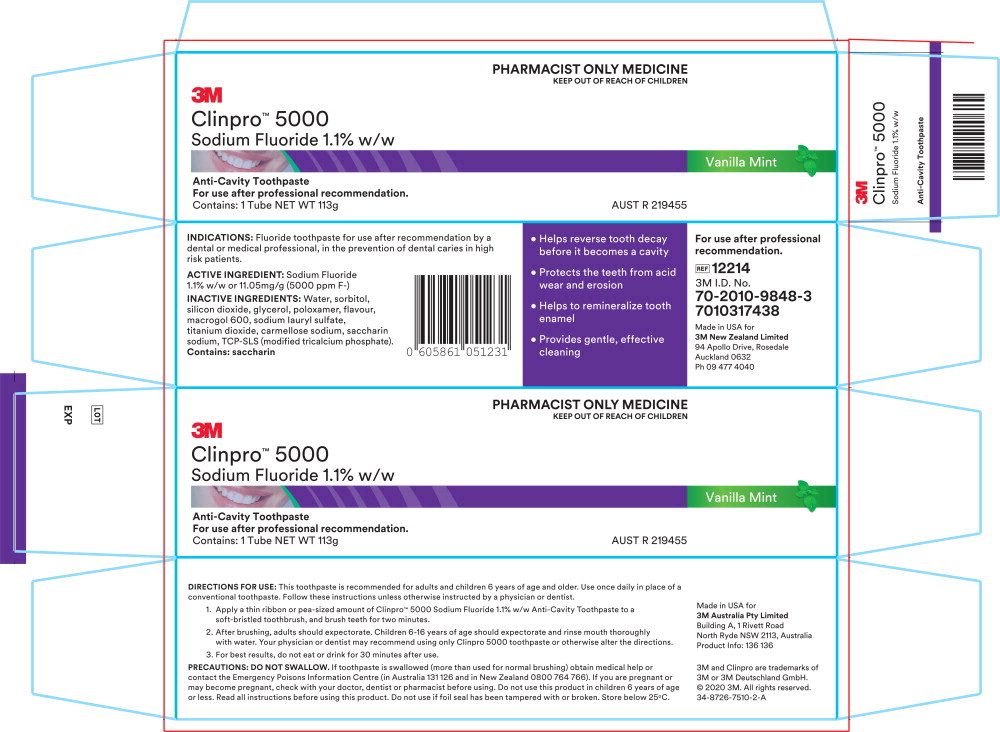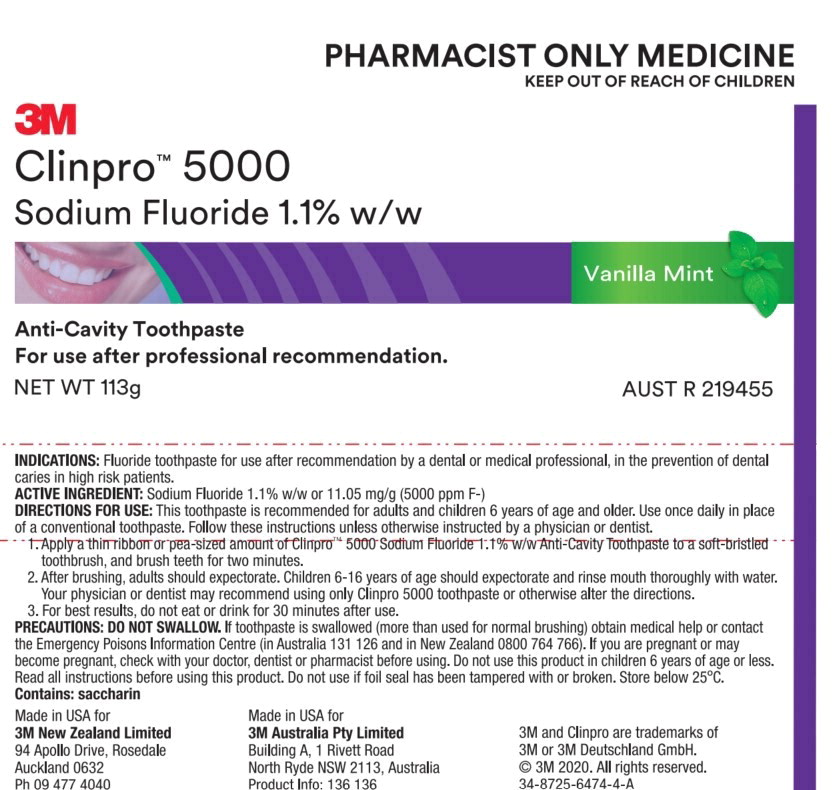 DRUG LABEL: Clinpro 5000
NDC: 48878-3120 | Form: PASTE, DENTIFRICE
Manufacturer: Solventum US LLC
Category: prescription | Type: HUMAN PRESCRIPTION DRUG LABEL
Date: 20240801

ACTIVE INGREDIENTS: sodium fluoride 5 mg/1 g
INACTIVE INGREDIENTS: Water; Sorbitol; Silicon Dioxide; Glycerin; Polyethylene Glycol, Unspecified; Sodium Lauryl Sulfate; Titanium Dioxide; Carboxymethylcellulose Sodium; Saccharin Sodium; Tricalcium Phosphate

Principal Display Panel – CA Box Label

3M ESPE

Clinpro MC 5000

Menthe-vanille

Dentifrice anticarie au

fluorure de sodium à 1,1 %

Formule de

diphosphate

tricalcique

novatrice

Offerte uniquement par 3M ESPE

Contenu : 1 tube POIDS NET : 113 g (4 oz)

NPN 80012416

Principal Display Panel – CA Tube Label

3M ESPE

Clinpro TM MC 5000

Vanilla Mint

Menthe vanilla

1.1% Sodium Fluoride Anti-Cavity Toothpaste

Dentifrice anticarie au flourure de sodium à 1,1 %

NET WT 113 g (4 oz) / POIDS NET : 133 g (4 oz)

NPN 80012416

Innovative

Tri-Calcium

Phosphate

Exclusively from 3M ESPE

Formule de

diphosphate

tricalcique

innovante

Offerte uniquement par 3M ESPE

Principal Display Panel – AU/NZ Box Label

PHARMACIST ONLY MEDICINE

KEEP OUT OF REACH OF CHILDREN

3M

Clinpro™ 5000

Sodium Fluoride 1.1% w/w

Vanilla Mint

Anti-Cavity Toothpaste

For use after professional recommendation.

Contains: 1 Tube NET WT 113g

AUST R 219455

Principal Display Panel – AU/NZ Tube Label

PHARMACIST ONLY MEDICINE

KEEP OUT OF REACH OF CHILDREN

3M

Clinpro™ 5000

Sodium Fluoride 1.1% w/w

Vanilla Mint

Anti-Cavity Toothpaste

For use after professional recommendation.

NET WT 113g

AUST R 219455